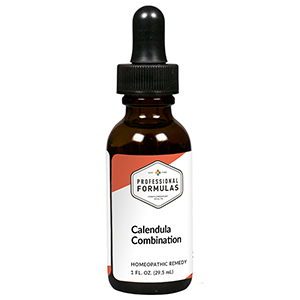 DRUG LABEL: Calendula Combination
NDC: 63083-9260 | Form: LIQUID
Manufacturer: Professional Complementary Health Formulas
Category: homeopathic | Type: HUMAN OTC DRUG LABEL
Date: 20190815

ACTIVE INGREDIENTS: BELLIS PERENNIS WHOLE 2 [hp_X]/29.5 mL; CALENDULA OFFICINALIS FLOWERING TOP 2 [hp_X]/29.5 mL; ECHINACEA ANGUSTIFOLIA WHOLE 2 [hp_X]/29.5 mL; HAMAMELIS VIRGINIANA ROOT BARK/STEM BARK 2 [hp_X]/29.5 mL; ACONITUM NAPELLUS WHOLE 3 [hp_X]/29.5 mL; ARNICA MONTANA WHOLE 3 [hp_X]/29.5 mL; ARTEMISIA ANNUA FLOWERING TOP 3 [hp_X]/29.5 mL; HYPERICUM PERFORATUM WHOLE 3 [hp_X]/29.5 mL; ACHILLEA MILLEFOLIUM WHOLE 3 [hp_X]/29.5 mL; AMARYLLIS BELLADONNA WHOLE 4 [hp_X]/29.5 mL; CALCIUM SULFIDE 5 [hp_X]/29.5 mL; COMFREY ROOT 6 [hp_X]/29.5 mL; ACTIVATED CHARCOAL 12 [hp_X]/29.5 mL; MERCURIUS SOLUBILIS 12 [hp_X]/29.5 mL
INACTIVE INGREDIENTS: ALCOHOL; WATER

R260

ACTIVE INGREDIENTS

Bellis perennis 2X
Calendula officinalis 2X
Echinacea angustifolia 2X
Hamamelis virginiana 2X
Aconitum napellus 3X
Arnica montana 3X
Chamomilla 3X
Hypericum perforatum 3X
Millefolium 3X
Belladonna 4X
Hepar sulphuris calcareum 5X
Symphytum officinale 6X
Carbo vegetabilis 12X
Mercurius solubilis 12X

QUESTIONS

Professional Formulas

PO Box 2034 Lake Oswego, OR 97035

INDICATIONS

For the temporary relief of mild pain, bruising, or swelling associated with minor injuries or wounds.*

PURPOSE

*Claims based on traditional homeopathic practice, not accepted medical evidence. Not FDA evaluated.

WARNINGS

If symptoms do not improve or are accompanied by a fever, consult a doctor. Keep out of the reach of children. In case of overdose, get medical help or contact a poison control center right away. If pregnant or breastfeeding, ask a healthcare professional before use.

Keep out of the reach of children.

PREGNANCY OR BREAST FEEDING

If pregnant or breastfeeding, ask a healthcare professional before use.

DIRECTIONS

Place drops under tongue 30 minutes before/after meals. Adults and children 12 years and over: Take 10 drops up to 3 times per day. Consult a physician for use in children under 12 years of age.

OTHER INFORMATION

Tamper resistant. If seal is broken, do not use. After opening, close container tightly and store at room temperature away from heat.

INACTIVE INGREDIENTS

40% ethanol, purified water.

LABEL

Est 1985

Professional Formulas

Complementary Health

Calendula Combination

Homeopathic Remedy

1 FL. OZ. (29.5 mL)